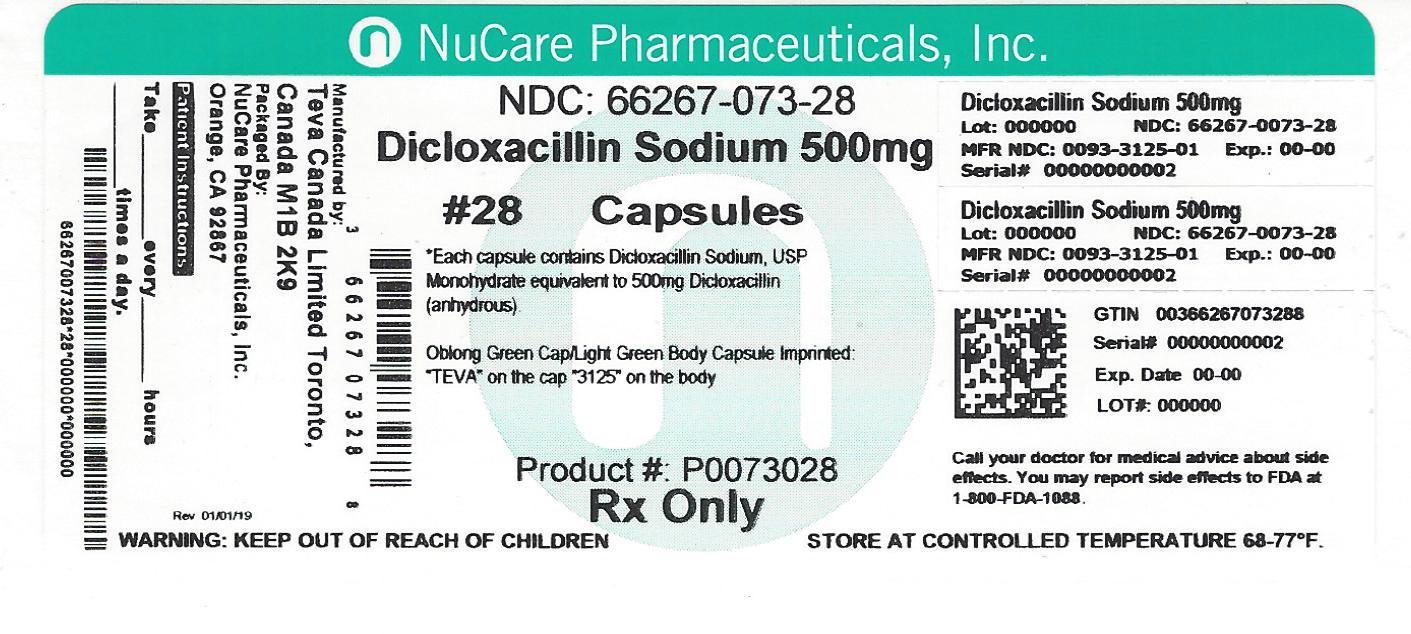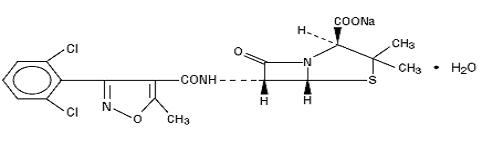 DRUG LABEL: Dicloxacillin Sodium
NDC: 66267-073 | Form: CAPSULE
Manufacturer: NuCare Pharmaceticals, Inc.
Category: prescription | Type: HUMAN PRESCRIPTION DRUG LABEL
Date: 20220113

ACTIVE INGREDIENTS: DICLOXACILLIN SODIUM 500 mg/1 1
INACTIVE INGREDIENTS: MAGNESIUM STEARATE; D&C YELLOW NO. 10; FD&C BLUE NO. 1; FD&C BLUE NO. 2; FD&C RED NO. 40; GELATIN; SHELLAC; SODIUM LAURYL SULFATE; SORBITAN MONOLAURATE; FERROSOFERRIC OXIDE; TITANIUM DIOXIDE; PROPYLENE GLYCOL

DICLOXACILLIN SODIUM CAPSULES USP
3123
3125
Rx only

To reduce the development of drug resistant bacteria and maintain the effectiveness of dicloxacillin sodium capsules USP and other antibacterial drugs, dicloxacillin sodium capsules USP should be used only to treat or prevent infections that are proven or strongly suspected to be caused by bacteria.

DESCRIPTION

Dicloxacillin sodium USP is a semisynthetic antibiotic substance which resists destruction by the enzyme penicillinase (beta - lactamase). It is monosodium (2 S,5 R,6 R)-6-[3-(2,6-dichlorophenyl)-5-methyl-4-isoxazolecarboxamido]-3,3-dimethyl-7-oxo-4-thia-1-azabicyclo [3.2.0]heptane-2-carboxylate monohydrate.

Dicloxacillin is administered orally via capsule form or powder for reconstitution. Structurally, dicloxacillin sodium USP may be represented as follows:

C19H16Cl2N3NaO5 S·H2O MW 510.32

CLINICAL PHARMACOLOGY

Microbiology

Mechanism of Action

Penicillinase-resistant penicillins exert a bactericidal action against penicillin-susceptible microorganisms during the state of active multiplication. All penicillins inhibit the biosynthesis of the bacterial cell wall.

Antibacterial Activity

Dicloxacillin sodium has been shown to be active against most isolates of the following microorganisms, both in vitro and in clinical infections as described in the INDICATIONS AND USAGE section.

Gram-positive Bacteria

Staphylococcus spp.

Susceptibility Test Methods

Susceptibility of staphylococcal isolates to dicloxacillin may be inferred by testing penicillin and either oxacillin or cefoxitin^1. For staphylococcal isolates, penicillin susceptibility implies susceptibility to other β-lactam agents, and penicillin resistance implies resistance to penicillinase-labile penicillins. Resistance to oxacillin (or cefoxitin) implies resistance to all other β-lactam agents, except newer agents with activity against methicillin-resistant Staphylococcus aureus. Routine testing of dicloxacillin is not advised.

Pharmacokinetics

Methicillin sodium is readily destroyed by gastric acidity and must be administered by intramuscular or intravenous injection. The isoxazolyl penicillins (cloxacillin, dicloxacillin and oxacillin) and nafcillin are more acid-resistant and may be administered orally.

Absorption of the isoxazolyl penicillins after oral administration is rapid but incomplete; peak blood levels are achieved in 1 to 1.5 hours. In one study, after ingestion of a single 500 mg oral dose, peak serum concentrations range from 5 to 7 micrograms/milliliter for oxacillin, from 7.5 to 14.4 mcg/mL for cloxacillin and from 10 to 17 mcg/mL for dicloxacillin.

Oral absorption of cloxacillin, dicloxacillin, oxacillin and nafcillin is delayed when the drugs are administered after meals.

Once absorbed, the penicillinase-resistant penicillins bind to serum protein, mainly albumin. The degree of protein binding reported varies with the method of study and the investigator (see TABLE II).

TABLE II PENICILLINASE-RESISTANT PENICILLINS PERCENT PROTEIN BINDING ± SD
Methicillin | 37.3 ± 7.9
Nafcillin | 89.9 ± 1.5
Oxacillin | 94.2 ± 2.1
Cloxacillin | 95.2 ± 0.5
Dicloxacillin | 97.9 ± 0.6

The penicillinase-resistant penicillins vary in the extent to which they are distributed in the body fluids. With normal doses, insignificant concentrations are found in the cerebrospinal fluid and aqueous humor. All the drugs in this class are found in therapeutic concentrations in the pleural, bile and amniotic fluids.

The penicillinase-resistant penicillins are rapidly excreted, primarily as unchanged drug in the urine by glomerular filtration and active tubular secretion. The elimination half-life for dicloxacillin is about 0.7 hour. Nonrenal elimination includes hepatic inactivation and excretion in bile.

INDICATIONS AND USAGE

To reduce the development of drug-resistant bacteria and maintain the effectiveness of dicloxacillin sodium capsules USP and other antibacterial drugs, dicloxacillin sodium capsules USP should be used only to treat or prevent infections that are proven or strongly suspected to be caused by susceptible bacteria. When culture and susceptibility information are available, they should be considered in selecting or modifying antibacterial therapy. In the absence of such data, local epidemiology and susceptibility patterns may contribute to the empiric selection of therapy.

Dicloxacillin is indicated in the treatment of infections caused by penicillinase-producing staphylococci which have demonstrated susceptibility to the drug. Cultures and susceptibility tests should be performed initially to determine the causative organisms and their sensitivity to the drug (see CLINICAL PHARMACOLOGY – Susceptibility Plate Testing) .

Dicloxacillin may be used to initiate therapy in suspected cases of resistant staphylococcal infections prior to the availability of laboratory test results. The penicillinase-resistant penicillins should not be used in infections caused by organisms susceptible to penicillin G. If the susceptibility tests indicate that the infection is due to an organism other than a resistant staphylococcus, therapy should not be continued with a penicillinase-resistant penicillin.

CONTRAINDICATIONS

A history of a hypersensitivity (anaphylactic) reaction to any penicillin is a contraindication.

WARNINGS

Serious and occasionally fatal hypersensitivity (anaphylactic shock with collapse) reactions have occurred in patients receiving penicillin. The incidence of anaphylactic shock in all penicillin-treated patients is between 0.015% and 0.04%. Anaphylactic shock resulting in death has occurred in approximately 0.002% of the patients treated. Although anaphylaxis is more frequent following a parenteral administration, it has occurred in patients receiving oral penicillins.

When penicillin therapy is indicated, it should be initiated only after a comprehensive patient drug and allergy history has been obtained. If an allergic reaction occurs, the drug should be discontinued and the patient should receive supportive treatment, e.g., artificial maintenance of ventilation, pressor amines, antihistamines and corticosteroids. Individuals with a history of penicillin hypersensitivity may also experience allergic reactions when treated with a cephalosporin.

PRECAUTIONS

General

Prescribing dicloxacillin sodium capsules in the absence of a proven or strongly suspected bacterial infection or a prophylactic indication is unlikely to provide benefit to the patient and increases the risk of the development of drug-resistant bacteria.

Dicloxacillin should generally not be administered to patients with a history of sensitivity to any penicillin.

Penicillin should be used with caution in individuals with histories of significant allergies and/or asthma. Whenever allergic reactions occur, penicillin should be withdrawn unless, in the opinion of the physician, the condition being treated is life-threatening and amenable only to penicillin therapy.

The oral route of administration should not be relied upon in patients with severe illness, or with nausea, vomiting, gastric dilatation, cardiospasm or intestinal hypermotility. Occasionally, patients will not absorb therapeutic amounts of orally administered penicillin.

The use of antibiotics may result in overgrowth of nonsusceptible organisms. If new infections due to bacteria or fungi occur, the drug should be discontinued and appropriate measures taken.

Information for the Patient

Patients should be counselled that antibacterial drugs including dicloxacillin sodium capsules should only be used to treat bacterial infections. They do not treat viral infections (e.g., the common cold). When dicloxacillin sodium capsules are prescribed to treat a bacterial infection, patients should be told that although it is common to feel better early in the course of therapy, the medication should be taken exactly as directed. Skipping doses or not completing the full course of therapy may (1) decrease the effectiveness of the immediate treatment and (2) increase the likelihood that bacteria will develop resistance and will not be treatable by dicloxacillin sodium capsules or other antibacterial drugs in the future.

Patients receiving penicillins should be given the following information and instructions by the physician:

1. Patients should be told that penicillin is an antibacterial agent which will work with the body’s natural defenses to control certain types of infections. They should be told that the drug should not be taken if they have had an allergic reaction to any form of penicillin previously, and to inform the physician of any allergies or previous allergic reactions to any drugs they may have had (see WARNINGS).
2. Patients who have previously experienced an anaphylactic reaction to penicillin should be instructed to wear a medical identification tag or bracelet.
3. Because most antibacterial drugs taken by mouth are best absorbed on an empty stomach, patients should be directed, unless circumstances warrant otherwise, to take penicillin one hour before meals or two hours after eating (see CLINICAL PHARMACOLOGY - Pharmacokinetics).
4. Patients should be told to take the entire course of therapy prescribed, even if fever and other symptoms have stopped (see PRECAUTIONS - General).
5. If any of the following reactions occur, stop taking your prescription and notify the physician: shortness of breath, wheezing, skin rash, mouth irritation, black tongue, sore throat, nausea, vomiting, diarrhea, fever, swollen joints or any unusual bleeding or bruising (see ADVERSE REACTIONS).
6. Do not take any additional medications without physician approval, including nonprescription drugs such as antacids, laxatives or vitamins.
7. Discard any liquid forms of penicillin after seven days if stored at room temperature or after 14 days if refrigerated.

Laboratory Tests

Bacteriologic studies to determine the causative organisms and their susceptibility to the penicillinase-resistant penicillins should be performed (see CLINICAL PHARMACOLOGY - Microbiology). In the treatment of suspected staphylococcal infections, therapy should be changed to another active agent if culture tests fail to demonstrate the presence of staphylococci.

Periodic assessment of organ system function, including renal, hepatic and hematopoietic, should be made during prolonged therapy with the penicillinase-resistant penicillins.

Blood cultures, white blood cell and differential cell counts should be obtained prior to initiation of therapy and at least weekly during therapy with penicillinase-resistant penicillins.

Periodic urinalysis, blood urea nitrogen and creatinine determinations should be performed during therapy with the penicillinase-resistant penicillins and dosage alterations should be considered if these values become elevated. If any impairment of renal function is suspected or known to exist, a reduction in the total dosage should be considered and blood levels monitored to avoid possible neurotoxic reactions (see DOSAGE AND ADMINISTRATION).

SGOT and SGPT values should be obtained periodically during therapy to monitor for possible liver function abnormalities.

Drug Interactions

Tetracycline, a bacteriostatic antibiotic, may antagonize the bactericidal effect of penicillin and concurrent use of these drugs should be avoided.

Carcinogenesis, Mutagenesis, Impairment of Fertility

No long-term animal studies have been conducted with these drugs.

Studies on reproduction (nafcillin) in rats and rabbits reveal no fetal or maternal abnormalities before conception and continuously through weaning (one generation).

Pregnancy Category B

Reproduction studies performed in the mouse, rat and rabbit have revealed no evidence of impaired fertility or harm to the fetus due to the penicillinase-resistant penicillins. Human experience with the penicillins during pregnancy has not shown any positive evidence of adverse effects on the fetus. There are, however, no adequate or well-controlled studies in pregnant women showing conclusively that harmful effects of these drugs on the fetus can be excluded. Because animal reproduction studies are not always predictive of human response, this drug should be used during pregnancy only if clearly needed.

Nursing Mothers

Penicillins are excreted in breast milk. Caution should be exercised when penicillins are administered to a nursing woman.

Pediatric Use

Because of incompletely developed renal function in newborns, penicillinase-resistant penicillins (especially methicillin) may not be completely excreted, with abnormally high blood levels resulting. Frequent monitoring of blood levels is advisable in this group, with dosage adjustments when necessary. All newborns treated with penicillins should be monitored closely for clinical and laboratory evidence of toxic or adverse effects (see DOSAGE AND ADMINISTRATION).

ADVERSE REACTIONS

Body as a Whole

The reported incidence of allergic reactions to penicillin ranges from 0.7% to 10% (see WARNINGS). Sensitization is usually the result of treatment, but some individuals have had immediate reactions to penicillin when first treated. In such cases, it is thought that the patients may have had prior exposure to the drug via trace amounts present in milk and vaccines.

Two types of allergic reactions to penicillin are noted clinically, immediate and delayed.

Immediate reactions usually occur within 20 minutes of administration and range in severity from urticaria and pruritus to angioneurotic edema, laryngospasm, bronchospasm, hypotension, vascular collapse and death. Such immediate anaphylactic reactions are very rare (see WARNINGS) and usually occur after parenteral therapy, but have occurred in patients receiving oral therapy. Another type of immediate reaction, an accelerated reaction, may occur between 20 minutes and 48 hours after administration and may include urticaria, pruritus and fever. Although laryngeal edema, laryngospasm and hypotension occasionally occur, fatality is uncommon.

Delayed allergic reactions to penicillin therapy usually occur after 48 hours and sometimes as late as two to four weeks after initiation of therapy. Manifestations of this type of reaction include serum sickness-like symptoms (i.e., fever, malaise, urticaria, myalgia, arthralgia, abdominal pain) and various skin rashes. Nausea, vomiting, diarrhea, stomatitis, black or hairy tongue and other symptoms of gastrointestinal irritation may occur, especially during oral penicillin therapy.

Nervous System Reactions

Neurotoxic reactions similar to those observed with penicillin G may occur with large intravenous doses of the penicillinase-resistant penicillins, especially with patients with renal insufficiency.

Urogenital Reactions

Renal tubular damage and interstitial nephritis have been associated with the administration of methicillin sodium and, infrequently, with the administration of nafcillin and oxacillin. Manifestations of this reaction may include rash, fever, eosinophilia, hematuria, proteinuria and renal insufficiency. Methicillin-induced nephropathy does not appear to be dose-related and is generally reversible upon prompt discontinuation of therapy.

Metabolic Reactions

Agranulocytosis, neutropenia and bone marrow depression have been associated with the use of methicillin sodium and nafcillin. Hepatotoxicity, characterized by fever, nausea and vomiting associated with abnormal liver function tests, mainly elevated SGOT levels, has been associated with the use of oxacillin.

RECOMMENDED DOSAGES FOR DICLOXACILLIN IN MILD TO MODERATE AND SEVERE INFECTIONS
DRUG | ADULTS |  | CHILDREN
 | Mild to Moderate | Severe | Mild to Moderate | Severe
Dicloxacillin | 125 mg every | 250 mg every | 12.5 mg/kg/day [Patients weighing less than 40 kg (88 lbs)] | 25 mg/kg/day
 | 6 hours | 6 hours | in equally | in equally
 |  |  | divided doses | divided doses
 |  |  | every 6 hours | every 6 hours

DOSAGE AND ADMINISTRATION

Bacteriologic studies to determine the causative organisms and their sensitivity to the penicillinase-resistant penicillins should always be performed. Duration of therapy varies with the type and severity of infection as well as the overall condition of the patient, therefore it should be determined by the clinical and bacteriological response of the patient. In severe staphylococcal infections, therapy with penicillinase-resistant penicillins should be continued for at least 14 days. Therapy should be continued for at least 48 hours after the patient has become afebrile, asymptomatic and cultures are negative. The treatment of endocarditis and osteomyelitis may require a longer term of therapy.

Concurrent administration of the penicillinase-resistant penicillins and probenecid increases and prolongs serum penicillin levels.

Probenecid decreases the apparent volume of distribution and slows the rate of excretion by competitively inhibiting renal tubular secretion of penicillin. Penicillin-probenecid therapy is generally limited to those infections where very high serum levels of penicillin are necessary.

Oral preparations of the penicillinase-resistant penicillins should not be used as initial therapy in serious, life-threatening infections (see PRECAUTIONS - General). Oral therapy with the penicillinase-resistant penicillins may be used to follow up the previous use of a parenteral agent as soon as the clinical condition warrants. For intramuscular gluteal injections, care should be taken to avoid sciatic nerve injury. With intravenous administration, particularly in elderly patients, care should be taken because of the possibility of thrombophlebitis.

NB: INFECTIONS CAUSED BY GROUP A BETA-HEMOLYTIC STREPTOCOCCI SHOULD BE TREATED FOR AT LEAST 10 DAYS TO HELP PREVENT THE OCCURRENCE OF ACUTE RHEUMATIC FEVER OR ACUTE GLOMERULONEPHRITIS.

HOW SUPPLIED

Dicloxacillin sodium capsules USP are available as follows:

500 mg: Each capsule contains dicloxacillin sodium monohydrate equivalent to 500 mg dicloxacillin (anhydrous), with green colored cap and light green colored body, imprinted "TEVA" on the cap and “3125” on the body, available in bottles of 28 (NDC 66267-073-28) and bottles of 30 (NDC 66267-073-30).

Store at 20° to 25°C (68° to 77°F) [See USP Controlled Room Temperature].

Dispense in a tight, light-resistant container as defined in the USP, with a child-resistant closure (as required).

KEEP THIS AND ALL MEDICATIONS OUT OF THE REACH OF CHILDREN.

REFERENCES

1. Clinical and Laboratory Standards Institute (CLSI). Performance Standards for Antimicrobial Susceptibility Testing; Twenty-fifth Informational Supplement. CLSI document M100-S25. Clinical and Laboratory Standards Institute, 950 West Valley Road, Suite 2500, Wayne, Pennsylvania 19087, USA, 2015.

Manufactured In Canada By:

TEVA CANADA LIMITED

Toronto, Canada M1B 2K9

Manufactured For:

TEVA PHARMACEUTICALS USA, INC.

North Wales, PA 19454

Rev. G 7/2015